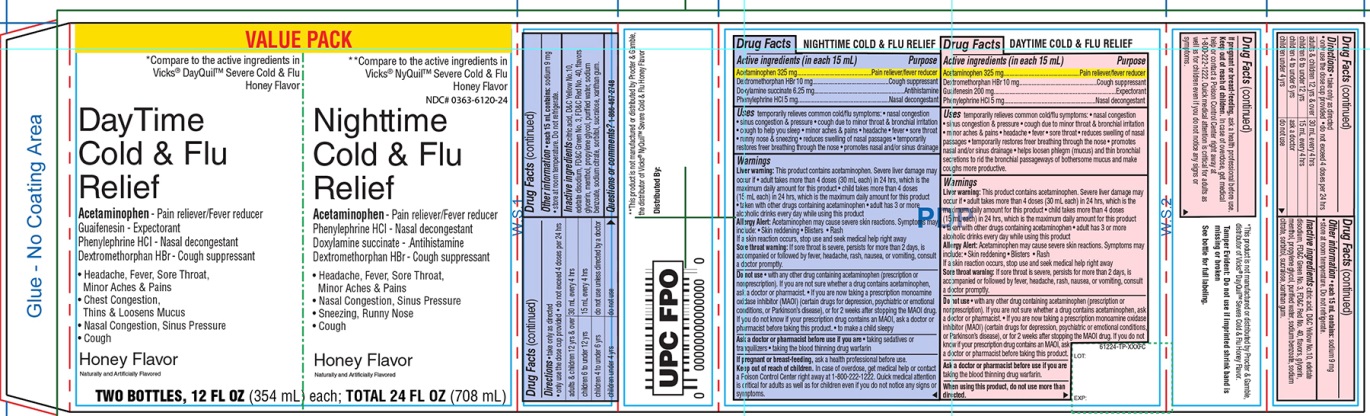 DRUG LABEL: Walgreen Day Time Nighttime Cold and Flu Relief
NDC: 0363-6120 | Form: KIT | Route: ORAL
Manufacturer: WALGREENS CO.
Category: otc | Type: HUMAN OTC DRUG LABEL
Date: 20210304

ACTIVE INGREDIENTS: ACETAMINOPHEN 325 mg/15 mL; DEXTROMETHORPHAN HYDROBROMIDE 10 mg/15 mL; DOXYLAMINE SUCCINATE 6.25 mg/15 mL; PHENYLEPHRINE HYDROCHLORIDE 5 mg/15 mL; ACETAMINOPHEN 325 mg/15 mL; DEXTROMETHORPHAN HYDROBROMIDE 10 mg/15 mL; GUAIFENESIN 200 mg/15 mL; PHENYLEPHRINE HYDROCHLORIDE 5 mg/15 mL
INACTIVE INGREDIENTS: ANHYDROUS CITRIC ACID; D&C YELLOW NO. 10; EDETATE DISODIUM; FD&C GREEN NO. 3; FD&C RED NO. 40; GLYCERIN; MENTHOL, UNSPECIFIED FORM; PROPYLENE GLYCOL; WATER; SODIUM BENZOATE; SODIUM CITRATE, UNSPECIFIED FORM; SORBITOL; SUCRALOSE; XANTHAN GUM; ANHYDROUS CITRIC ACID; D&C YELLOW NO. 10; EDETATE DISODIUM; FD&C GREEN NO. 3; FD&C RED NO. 40; GLYCERIN; MENTHOL, UNSPECIFIED FORM; PROPYLENE GLYCOL; WATER; SODIUM BENZOATE; SODIUM CITRATE, UNSPECIFIED FORM; SORBITOL; SUCRALOSE; XANTHAN GUM

Walgreen DayTime NightTime Cold & Flu Relief Drug Facts

Active ingredients (in each 15 mL) – NightTime

Acetaminophen 325 mg

Dextromethorphan HBr 10 mg

Doxylamine succinate 6.25 mg

Phenylephrine HCl 5 mg

Purpose

Pain reliever/fever reducer

Cough suppressant

Antihistamine

Nasal decongestant

Uses

temporarily relieves common cold/flu symptoms:

- nasal congestion
- sinus congestion and pressure
- minor aches and pains
- headache
- fever
- sore throat
- runny nose and sneezing
- cough due to minor throat and bronchial irritation
- cough to help you sleep
- reduces swelling of nasal passages
- promotes nasal and/or sinus drainage
- temporarily restores freer breathing through the nose

Warnings

Liver warning: This product contains acetaminophen. Severe liver damage may occur if you take

- more than 4 doses in 24 hours, which is the maximum daily amount for this product
- with other drugs containing acetaminophen
- 3 or more alcoholic drinks every day while using this product

Allergy alert: Acetaminophen may cause severe skin reactions. Symptoms may include:

- Skin reddening
- Blisters
- Rash

If a skin reaction occurs, stop use and seek medical help right away.

Sore throat warning: If sore throat is severe, persists for more than 2 days, is accompanied or followed by fever, headache, rash, nausea, or vomiting, consult a doctor promptly.

Do not use

- with any other drug containing acetaminophen (prescription or nonprescription). If you are not sure whether a drug contains acetaminophen, ask a doctor or pharmacist.
- if you are now taking a prescription monoamine oxidase inhibitor (MAOI) (certain drugs for depression, psychiatric, or emotional conditions, or Parkinson’s disease), or for 2 weeks after stopping the MAOI drug. If you do not know if your prescription drug contains an MAOI, ask a doctor or pharmacist before taking this product.
- to make child sleepy

Ask a doctor or pharmacist before use if you are

- taking sedatives or tranquilizers
- taking the blood thinning drug warfarin.

If pregnant or breast-feeding, ask a health professional before use

Keep out of reach of children.

In case of overdose, get medical help or contact a Poison Control Center right away at 1-800-222-1222. Quick medical attention is critical for adults as well as for children even if you do not notice any signs or symptoms.

Directions

- take only as directed
- only use the dose cup provided
- do not exceed 4 doses per 24 hrs

adults & children 12 yrs & over | 30 mL every 4 hrs
children 6 to under 12 yrs | 15mL every 4 hrs
children under 4 to under 6 yrs | do not use unless directed by a doctor
Children under 4 yrs | Do not use

Other information

- each 15 mL contains: sodium 9 mg
- store at room temperature
- Do not refrigerate

Inactive ingredients

citric acid, D&C yellow #10, edetate disodium, FD&C Green No 3, FD&C Red No.40, flavors, glycerin, menthol, propylene glycol, purified water, sodium benzoate, sodium citrate, sorbitol, sucralose, xanthan gum

Questions or comments?

1-866-467-2748

Active ingredients (in each 15 mL) - Day Time

Acetaminophen 325 mg

Dextromethorphan HBr 10 mg

Guaifenesin 200 mg

Phenylephrine HCl 5 mg

Purpose

Pain reliever/fever reducer

Cough suppressant

Expectorant

Nasal decongestant

Uses

temporarily relieves common cold/flu symptoms:

- nasal congestion
- sinus congestion and pressure
- cough due to minor throat and bronchial irritation
- minor aches and pains
- headache
- fever
- sore throat
- reduces swelling of nasal passages
- temporarily restores freer breathing through the nose
- promotes nasal and/or sinus drainage
- helps loosen phlegm (mucus) and thin bronchial secretions to rid the bronchial passageways of bothersome mucus and make coughs more productive

Warnings

Liver warning: This product contains acetaminophen. Severe liver damage may occur if you take

- more than 4 doses in 24 hours, which is the maximum daily amount for this product.
- with other drugs containing acetaminophen
- 3 or more alcoholic drinks every day while using this product

Allergy alert: Acetaminophen may cause severe skin reactions. Symptoms may include:

- Skin reddening
- Blisters
- Rash

If a skin reaction occurs, stop use and seek medical help right away.

Sore throat warning: If sore throat is severe, persists for more than 2 days, is accompanied or followed by fever, headache, rash, nausea, or vomiting, consult a doctor promptly.

Do not use

- with any other drug containing acetaminophen (prescription or nonprescription). If you are not sure whether a drug contains acetaminophen, ask a doctor or pharmacist.
- if you are now taking a prescription monoamine oxidase inhibitor (MAOI) (certain drugs for depression, psychiatric, or emotional conditions, or Parkinson’s disease), or for 2 weeks after stopping the MAOI drug. If you do not know if your prescription drug contains an MAOI, ask a doctor or pharmacist before taking this product.

When using this product

do not use more than directed

If pregnant or breast-feeding,

ask a health professional before use.

Keep out of reach of children.

Overdose warning: In case of overdose, get medical help or contact a Poison Control Center right away at (1-800-222-1222). Quick medical attention is critical for adults as well as for children even if you do not notice any signs or symptoms.

Directions

- take only as directed
- only use the dose cup provided
- do not exceed 4 doses per 24 hrs

adults & children 12 yrs & over | 30 mL every 4 hrs
children 6 to under 12 yrs | 15mL every 4 hrs
children under 4 to under 6 yrs | ask a doctor
Children under 4 yrs | do not use

Other information

- each 15 mL contains: sodium 9 mg
- store at room temperature.
- Do not refrigerate.

Inactive ingredients

citric acid, D&C yellow #10, edetate disodium,

FD&C Green #3, FD&C Red No. 40, flavors, glycerin, menthol, propylene glycol, purified water, sodium benzoate, sodium citrate, sorbitol, sucralose, xanthan gum

Package/Label Principal Display Panel

VALUE PACK

*Compare to the active ingredients in Vicks® Dayquil™ Severe cold & Flu Honey Flavor

DayTime

Cold & Flu

Relief

Acetaminophen - Pain reliever / Fever reducer

Guaifenesin - Expectorant

Phenylephrine HCl - Nasal decongestant

Dextromethorphan HBr - Cough supressant

- Headache, Fever, sore Throat, Minor Aches & Pains
- Chest Congestion Thins & Loosen Mucus
- Nasal Congestion & Sinus Pressure
- Cough

Honey Flavor

Naturally and Artificially Flavored

TWO BOTTLES, 12 FL OZ (354 mL)

**Compare to the active ingredients in Vicks® Nyquil™ Severe cold & Flu Honey Flavor

Nighttime

Cold & Flu

Relief

Acetaminophen - Pain reliever / Fever reducer

Phenylephrine HCl - Nasal decongestant

Doxylamine succinate - Antihistamine

Dextromethorphan HBr - Cough supressant

For Relief of

- Headache, Fever, Sore Throat, Minor Aches & Pains,
- Nasal Congestion & Sinus Pressure
- Sneezing, Runny Nose
- Cough

Honey Flavor

Naturally and Artificially Flavored

Each; TOTAL 24 FL OZ (708 mL)